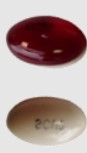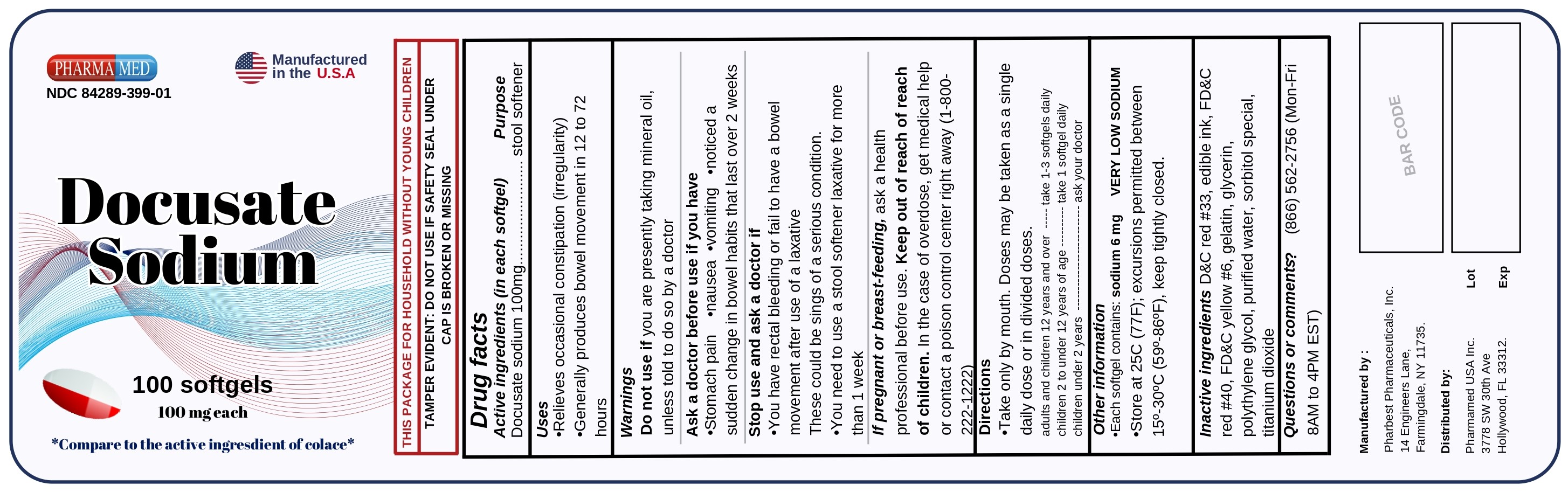 DRUG LABEL: Docusate Sodium
NDC: 84289-399 | Form: CAPSULE
Manufacturer: PHARMAMED USA INC
Category: otc | Type: HUMAN OTC DRUG LABEL
Date: 20240626

ACTIVE INGREDIENTS: DOCUSATE SODIUM 100 mg/1 1
INACTIVE INGREDIENTS: D&C RED NO. 33; FD&C RED NO. 40; SORBITOL; TITANIUM DIOXIDE; GLYCERIN; FD&C YELLOW NO. 6; POLYETHYLENE GLYCOL, UNSPECIFIED; WATER; GELATIN, UNSPECIFIED

Docusate Sodium 100 mg Softgels

Active ingredient (in each softgel)

Docusate Sodium 100 mg

Purpose

Stool softener

Uses

- relieves occasional constipation (irregularity)
- generally produces bowel movement in 12 to 72 hours

Warnings

Do not use if you are presently taking mineral oil, unless told to do so by a doctor

Ask a doctor before use if you have

- stomach pain
- nausea
- vomiting
- noticed a sudden change in bowel habits that lasts over 2 weeks

Stop use and ask a doctor if

- you have rectal bleeding or fail to have bowel movement after use of a laxative. These could be signs of a serious condition.
- you need to use a stool softener laxative for more than 1 week

If pregnant or breast-feeding,

ask a health professional before use.

Keep out of reach of children.

In case of overdose, get medical help or contact a Poison Control Center right away. (1 800-222-1222)

Directions

- Take only by mouth. Doses may be taken as a single daily dose or in divided doses.

adults and children 12 years and over | take 1-3 softgels daily
children 2 to under 12 years of age | take 1 softgel daily
children under 2 years | ask a doctor

Other information

- each softgel contains: sodium 6 mg
- VERY LOW SODIUM
- store at 25ºC (77ºF); excursions permitted between 15º-30ºC (59º-86ºF).

keep tightly closed.

Inactive ingredients

D&C Red #33, edible ink, FD&C Red #40, FD&C Yellow #6, gelatin, glycerin, polyethylene glycol, purified water, sorbitol special, titanium dioxide

Questions or comments?

(866) 562-2756 (Mon-Fri 8 AM to 4 PM EST)

Package Label Principal Display Panel

PHARMAMED

NDC 84289-399-01

Manufactured in the U.S.A

Docusate

Sodium

100 softgels

100mg each

*Compare to the active ingredient of Colace*

THIS PACKAGE FOR HOUSEHOLD WITHOUT YOUNG CHILDREN

TAMPER EVIDENT: DO NOT USE IF SAFETY SEAL UNDER CAP IS BROKEN OR MISSING